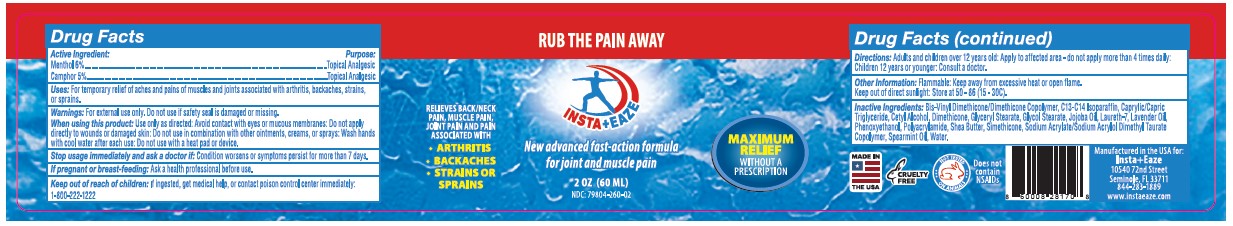 DRUG LABEL: Pain Cream
NDC: 79804-260 | Form: CREAM
Manufacturer: Eagle Labs Inc.
Category: otc | Type: HUMAN OTC DRUG LABEL
Date: 20240415

ACTIVE INGREDIENTS: MENTHOL 0.06 g/1 g; CAMPHOR (SYNTHETIC) 0.05 g/1 g
INACTIVE INGREDIENTS: CETYL DIMETHICONE/BIS-VINYLDIMETHICONE CROSSPOLYMER; CAPRYLIC/CAPRIC ACID; WATER; CETYL ALCOHOL; SODIUM ACRYLATE/SODIUM ACRYLOYLDIMETHYLTAURATE COPOLYMER (4000000 MW); PHENOXYETHANOL; SHEA BUTTER; SILICON DIOXIDE; LAURETH-7; LAVENDER OIL; SPEARMINT OIL; C13-14 ISOPARAFFIN; DIMETHICONE; GLYCOL STEARATE; JOJOBA OIL

Pain Cream

Active Ingredient

Menthol 6%

Camphor 5%

Purpose

Topical Analgesic

Uses:

For Temporary relief of aches and pains of muscles and joints associated with arthritis, bachaches, strains, or sprains.

WARNINGS:

For external use only. Do not use if safety seal is damaged or missing.

WHEN USING THIS PRODUCT

Use only as directed: Avoid contact with eyes or mucous membranes: Do not apply directly to wounds or damaged skin: Do no use in combination with other ointments, creams, or sprays: Wash hands with cool water after each use: Do not sue with a heat pad or device.

Stop Usage immediately and as a doctor if:

Condition worsens or symptoms persist for more than 7 days.

If pregnant or breast-feeding:

Ask a health professional before use

Keep out of reach of children

If ingested, get medical help, or contact poison control center immediately: 1-800-222-1222

Directions:

Adults and children over 12 years old: Apply to affected area - do not apply more than 4 times adaily: Children 12 years or younger: Consult a doctor

Other Information

Flammable: Keep away from excessive heat or open flame. Keep out of direct sunlight: Store at 50-86F (15-30C)

Inactive Ingredients:

Bis-Vinyl Dimethicone/Dimthicone Copolymer, C13-C14 Isoparaffin, Caprylic/Capric Triglyceride, Cetyl Alcohol, Dimethicone, Glyceryl Stearate, Glycol Stearate, Jojoba Oil, Laureth-7, Lavender Oil, Phenoxyethanol, Polyarylamide, Shea Butter, Simethicone, Sodium Acrylate/Sodium Acrylol Dimethyl Taurate Copolymer, Spearmint Oil, Water.